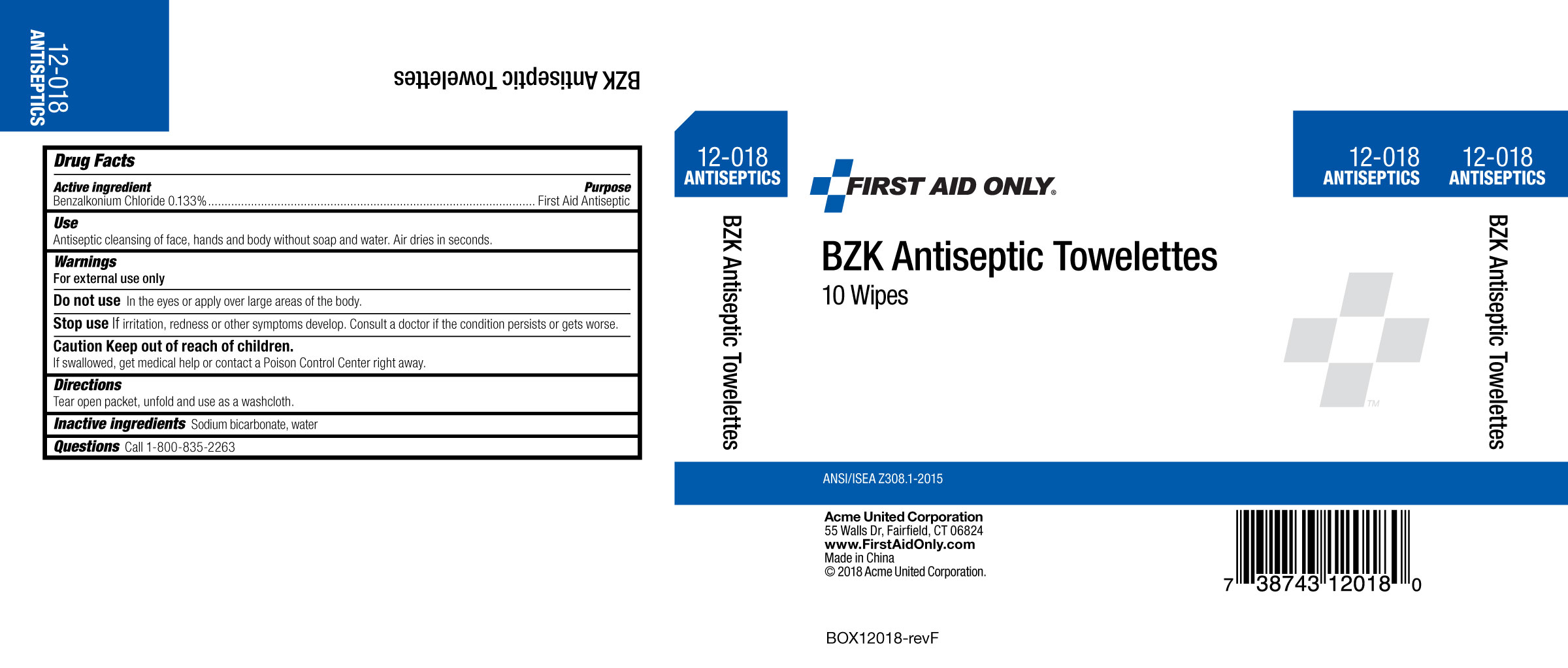 DRUG LABEL: BZK Towelette
NDC: 0924-7112 | Form: SWAB
Manufacturer: Acme United Corporation
Category: otc | Type: HUMAN OTC DRUG LABEL
Date: 20190416

ACTIVE INGREDIENTS: BENZALKONIUM CHLORIDE 1.33 mg/1 mL
INACTIVE INGREDIENTS: WATER

Firsat Aid Only BZK Antiseptic Towelettes

Drug Facts

Active Ingredients

Benzalkonium Chloride, 0.133% w/v

Purpose

First Aid Antiseptic

Use

Antiseptic Cleansing of face, hands and body without soap and water. Air dries in seconds.

Do Not Use

In the eyes or apply over large areas of the body.

Stop Use

If irritation, redness or other symptoms develop. Consult a doctor if the condition persists or gets worse.

Caution

Keep out of reach of children.

If swallowed, get medical help or contact a Poison Control Center right away.

Directions

Tear open packet, unfold and use as a washcloth.

Inactive Ingredients

Sodium Bicarbonate, Water

Principal Display Panel - 1.4 mL Pouch Label

Carton Image